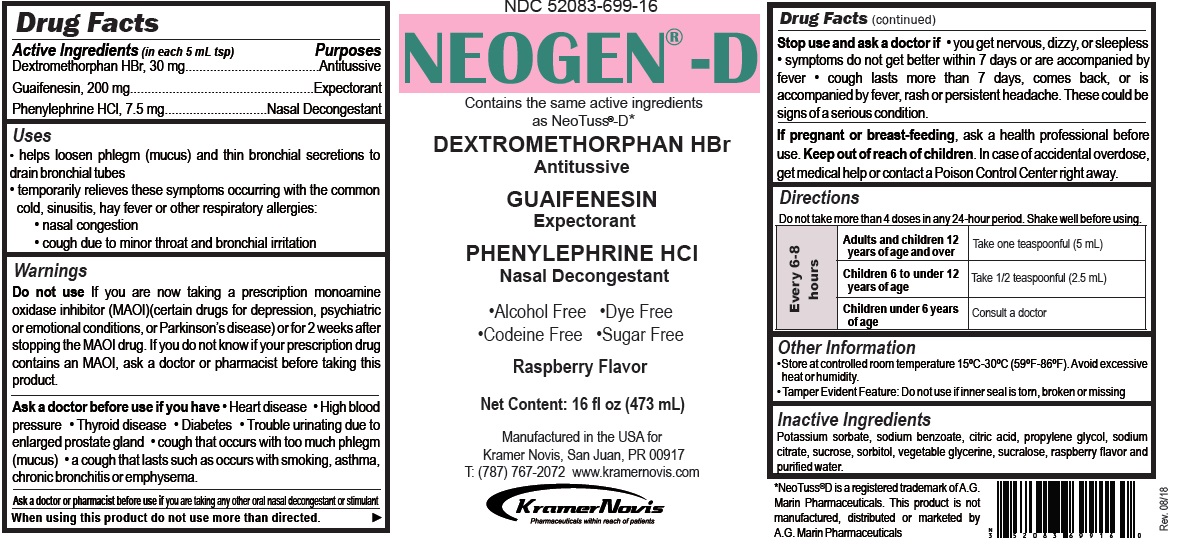 DRUG LABEL: NEOGEN-D
NDC: 52083-699 | Form: SOLUTION
Manufacturer: Kramer Novis
Category: otc | Type: HUMAN OTC DRUG LABEL
Date: 20181122

ACTIVE INGREDIENTS: DEXTROMETHORPHAN HYDROBROMIDE 30 mg/5 mL; GUAIFENESIN 200 mg/5 mL; PHENYLEPHRINE HYDROCHLORIDE 7.5 mg/5 mL
INACTIVE INGREDIENTS: POTASSIUM SORBATE; SODIUM BENZOATE; CITRIC ACID MONOHYDRATE; PROPYLENE GLYCOL; SODIUM CITRATE, UNSPECIFIED FORM; SUCROSE; SORBITOL; GLYCERIN; SUCRALOSE; WATER

NEOGEN® -D

Active Ingredients (in each 5 mL tsp)

Dextromethorphan HBr, 30 mg

Guaifenesin, 200 mg

Phenylephrine HCL, 7.5 mg

Purposes

Antitussive

Expectorant

Nasal Decongestant

Uses

• helps loosen phlegm (mucus) and thin bronchial secretions to drain bronchial tubes.

• temporarily relieves these symptoms occurring with the common cold, sinusitis, hay fever or other respiratory allergies.

• nasal congestion

• cough due to minor throat and bronchial irritation

Warnings

Do not use If you are now taking a prescription monoamine oxidase inhibitor (MAOI)(certain drugs for depression, psychiatric or emotional conditions, or Parkinson's disease) or for 2 weeks after stopping the MAOI drug. If you do not know if your prescription drug contains an MAOI, ask a doctor or pharmacist before taking this product.

Ask a doctor before use if you have

• Heart disease • High blood pressure • Thyroid disease • Diabetes • Trouble urinating due to enlarged prostate gland • cough that occurs with too much phlegm (mucus) • a cough that lasts such as occurs with smoking, asthma, chronic bronchitis or emphysema.

Ask a doctor or pharmacist before use if you are taking any other oral nasal decongestant or stimulant.

When using this product do not use more than directed.

Stop use and ask a doctor if • you get nervous, dizzy, or sleepless • symptoms do not get better within 7 days or are accompanied by fever • cough lasts more than 7 days, comes back, or is accompanied by fever, rash or persistent headache. These could be signs of a serious condition.

If pregnant or breast-feeding, ask a health professional before use.

Keep out of reach of children. In case of accidental overdose, get medical help or contact a Poison Control Center right away.

Directions

Do not take more than 4 doses in any 24-hour period. Shake well before using.

Every 6-8 hours | Adults and children 12 years of age and over | Take one teaspoonful (5 mL)
Every 6-8 hours | Children 6 to under 12 years of age | Take 1/2 teaspoonful (2.5 mL)
Every 6-8 hours | Children under 6 years of age | Consult a doctor

Other Information

• Store at controlled room temperature 15°C-30°C (59°F-86°F). Avoid excessive heat or humidity.

• Tamper Evident Feature: Do not use if inner seal is torn, broken or missing.

Inactive Ingredients

Potassium sorbate, sodium benzoate, citric acid, propylene glycol, sodium citrate, sucrose, sorbitol, vegetable glycerin, sucralose, raspberry flavor and purified water

Contains the same active ingredients as Neo Tuss®-D*

DEXTROMETHORPHAN HBr
Antitussive

GUAIFENESIN
Expectorant

PHENYLEPHRINE HCL
Nasal Decongestant

• Alcohol Free • Dye Free

• Codeine Free • Sugar Free

Raspberry Flavor

Manufactured in the USA for Kramer Novis, San Juan, PR 00917.

T:(787) 767-2072 www.kramernovis.com

* Neo Tuss®-D* is a registered trademark of A.G. Marin Pharmaceuticals. This product is not manufactured, distributed or marketed by A.G. Marin Pharmaceuticals.